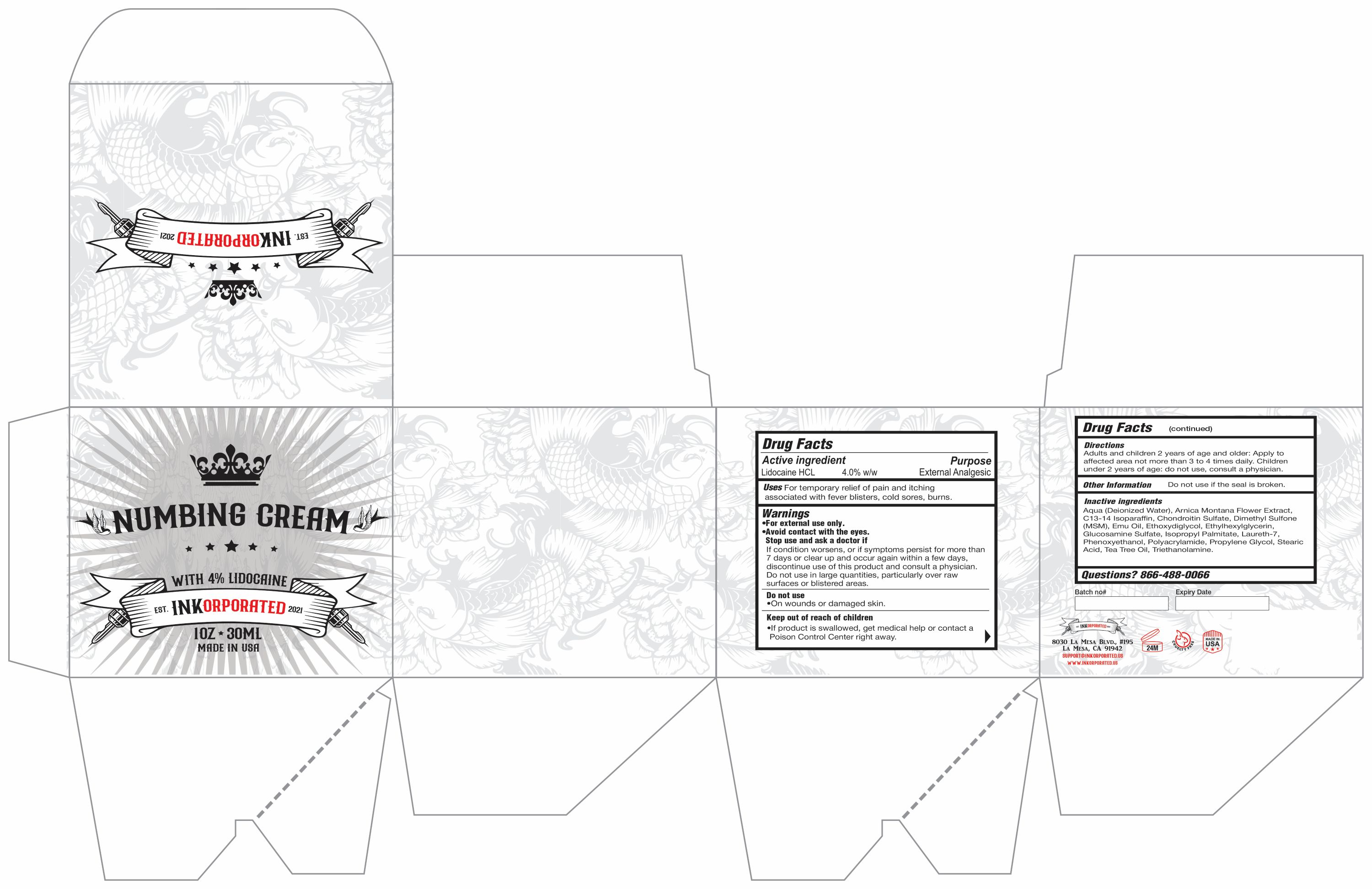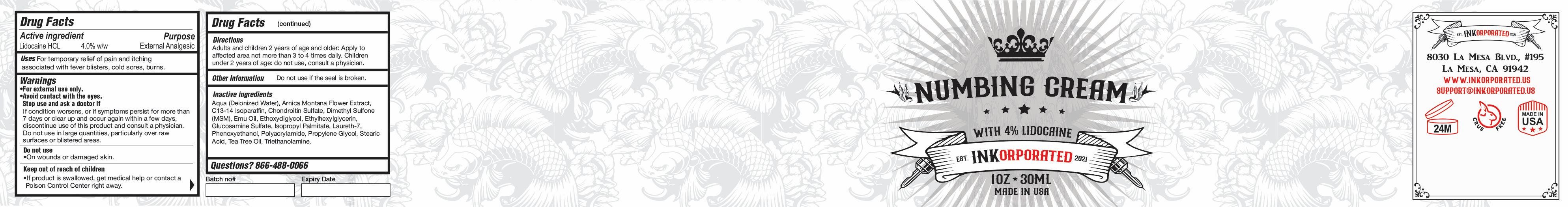 DRUG LABEL: Inkorporated Numbing
NDC: 70171-0028 | Form: CREAM
Manufacturer: Prodigy Media Inc
Category: otc | Type: HUMAN OTC DRUG LABEL
Date: 20250917

ACTIVE INGREDIENTS: LIDOCAINE HYDROCHLORIDE 4 g/100 g
INACTIVE INGREDIENTS: WATER; ARNICA MONTANA FLOWER; C13-14 ISOPARAFFIN; ELOSULFASE ALFA; DIMETHYL SULFONE; EMU OIL; DIETHYLENE GLYCOL MONOETHYL ETHER; ETHYLHEXYLGLYCERIN; GLUCOSAMINE SULFATE; ISOPROPYL PALMITATE; LAURETH-7; PHENOXYETHANOL; POLYACRYLAMIDE (CROSSLINKED; 2 MOLE PERCENT BISACRYLAMIDE); PROPYLENE GLYCOL; STEARIC ACID; TEA TREE OIL

Active Ingredient

Lidocaine HCL 4%

Purpose

External Analgesic

Uses

For the temporary relief of pain and itching associated with sunburns, minor cuts, insect bites, and skin irritations

Warnings

- For external use only.
- Avoid contact with eyes

Stop use and ask a doctor if

- Condition worsens or symptoms persist for more than 7 days
- Symptoms clear up and occur again within a few days
- Do not use in large quantities, particularly over raw surfaces or blistered areas. Do not exceed the recommended daily dosage unless directed by a doctor.

Do not use

- On wounds or damaged skin.

Keep out of reach of children

If product is swallowed, get medical help or contact a Poison Control Center right away.

Direction

Adults and children 2 years of age and older: Apply to affected area not more than 3 to 4 times daily. Children under 2 years of age: do not use, consult a physician.

Other information

Do not use if seal is broken.

Inactive ingredients

Aqua (Deionized Water), Arnica Montana Flower Extract,C13-14 Isoparaffin, Chondroitin Sulfate, Dimethyl Sulfone (MSM), Emu Oil,
Ethoxydiglycol, Ethylhexylglycerin, Glucosamine Sulfate, Isopropyl Palmitate, Laureth-7, Phenoxyethanol, Polyacrylamide, Propylene Glycol, Stearic Acid,Tea Tree Oil, Triethanolamine.

Questions? 866-488-0066

Product label

INKD Lido Label.jpg

INKD Lido Box.jpg